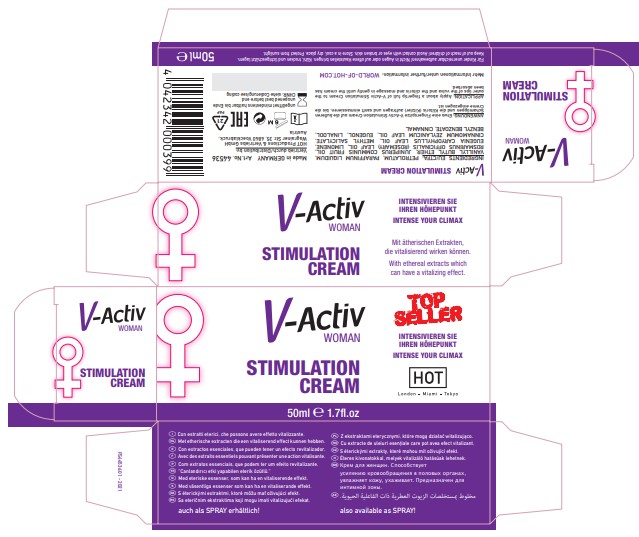 DRUG LABEL: V-ACTIV FOR WOMEN
NDC: 71326-206 | Form: CREAM
Manufacturer: HOT PRODUCTIONS AND VERTRIEBS GMBH
Category: homeopathic | Type: HUMAN OTC DRUG LABEL
Date: 20231005

ACTIVE INGREDIENTS: CINNAMON LEAF OIL 0.1 g/100 mL
INACTIVE INGREDIENTS: EUGENOL; ROSEMARY OIL; MINERAL OIL; METHYL SALICYLATE; VANILLYL BUTYL ETHER; CLOVE LEAF OIL; JUNIPER BERRY OIL; BENZYL BENZOATE; LINALOOL, (+)-; CINNAMALDEHYDE; LIMONENE, (+)-; PETROLATUM

HOT PRODUCTS - V-ACTIV FOR WOMEN CREAM (71326-206)

ACTIVE INGREDIENTS

CINNAMOMUM ZEYLANICUM LEAF OIL 0.1X HPUS

PURPOSE

Topical stimulation

USE

STIMULATION CREAM

WARNINGS

Avoid contact with the eyes or broken skin.

Keep out of reach of children. If product is accidentally swallowed, get medical help or contact a Poison Control Center right away.

APPLICATION

Apply about a fingertip full of V-Activ Stimulation Cream to the outer lips of the vulva and the clitoris and massage in gently until the cream has been absorbed.

OTHER INFORMATION

- Store in a cool, dry place. Protect from sunlight.

INACTIVE INGREDIENTS

PETROLATUM, PARAFFINUM LIQUIDUM, VANILLYL BUTYL ETHER, JUNIPERUS COMMUNIS FRUIT OIL, ROSMARINUS OFFICINALIS (ROSEMARY) LEAF OIL, LIMONENE, EUGENIA CARYOPHYLLUS LEAF OIL, METHYL SALICYLATE,
CINNAMOMUM ZEYLANICUM LEAF OIL, EUGENOL, LINALOOL, BENZYL BENZOATE, CINNAMAL